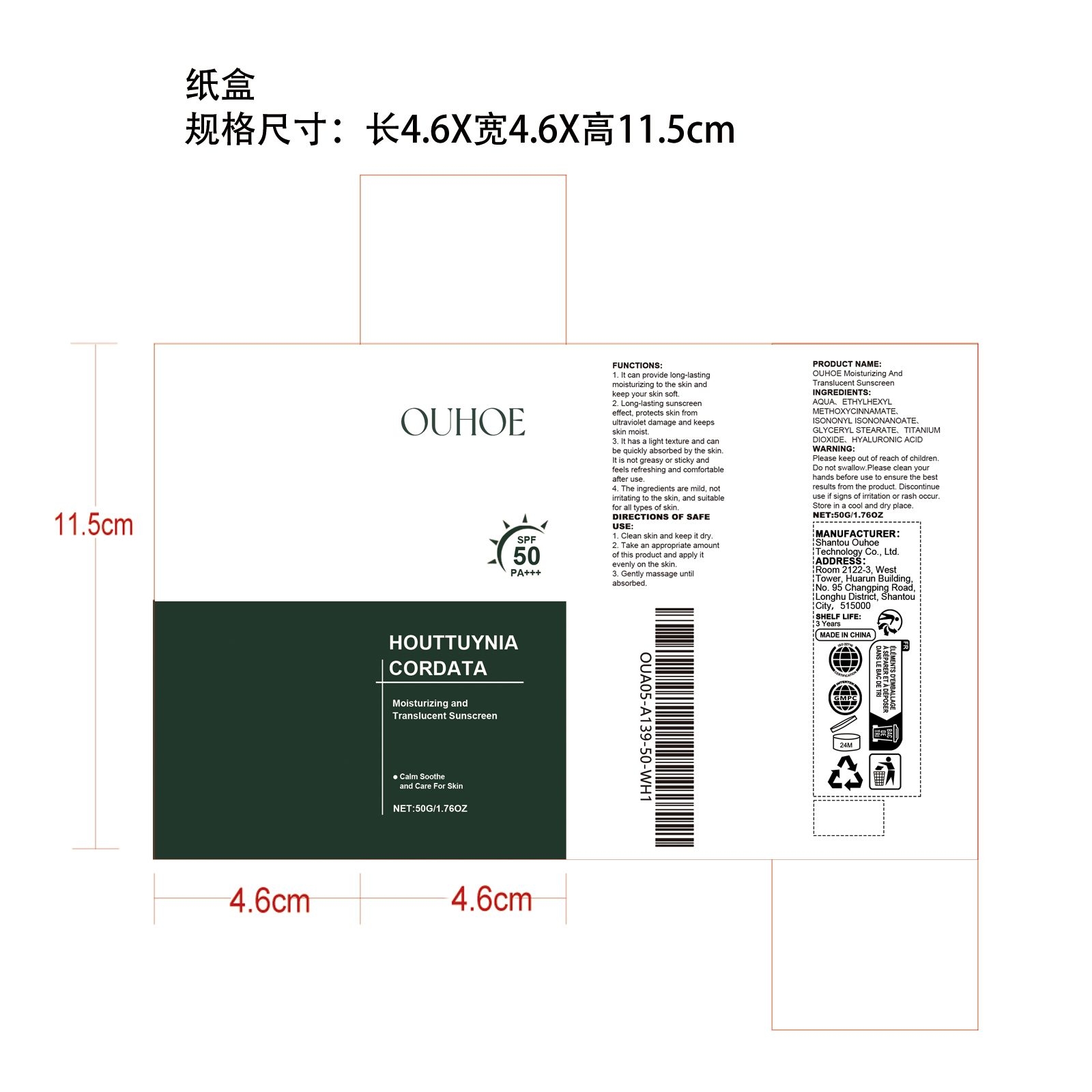 DRUG LABEL: OUHOE Moisturizing And Translucent Sunscreen
NDC: 85163-005 | Form: CREAM
Manufacturer: Shantou Ouhoe Technology Co., Ltd.
Category: otc | Type: HUMAN OTC DRUG LABEL
Date: 20251127

ACTIVE INGREDIENTS: CENTELLA ASIATICA 0.01 mg/50 mg
INACTIVE INGREDIENTS: AQUA 44.14 mg/50 mg; ETHYLHEXYL METHOXYCINNAMATE 2.5 mg/50 mg; TITANIUM DIOXIDE 0.6 mg/50 mg; GLYCERYL STEARATE 0.75 mg/50 mg; ISONONYL ISONONANOATE 2 mg/50 mg

ACTIVE INGREDIENT

CENTELLA ASIATICA

PURPOSE

1. It can provide long-lasting moisturizing to the skin and keep your skin soft.

2. Long-lasting sunscreen effect, protects skin from ultraviolet damage and keeps skin moist.

3. It has a light texture and can be quickly absorbed by the skin. It is not greasy or sticky and feels refreshing and comfortable after use.

4. The ingredients are mild, not irritating to the skin, and suitable for all types of skin.

WHEN USING

1. Clean skin and keep it dry

2. Take an appropriate amount of this product and apply it evenly on the skin

3. Gently massage until absorbed.

WARNINGS

Please keep out of reach of children. Do not swallow.Please clean your hands before use to ensure the best results from the product. Discontinue use if signs of irritation or rash occur. Store in a cool and dry place.

DO NOT USE

Discontinue use if signs of irritation or rash occur.

STOP USE

Discontinue use if signs of irritation or rash occur.

KEEP OUT OF REACH OF CHILDREN

Please keep out of reach of children. Do not swallow.

STORAGE AND HANDLING

Store in a cool and dry place.

INACTIVE INGREDIENT

AQUA
ETHYLHEXYL METHOXYCINNAMATE
ISONONYL ISONONANOATE
GLYCERYL STEARATE
TITANIUM DIOXIDE